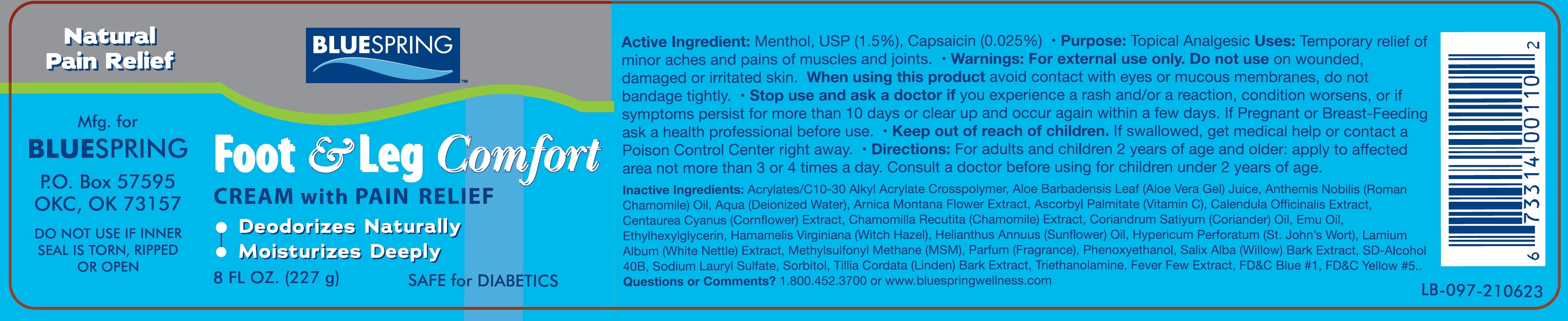 DRUG LABEL: BLUE SPRING Foot and Leg Comfort Cream with Pain Relief
NDC: 14448-316 | Form: CREAM
Manufacturer: BLUE SPRING WELLNESS, L.L.C.
Category: otc | Type: HUMAN OTC DRUG LABEL
Date: 20231110

ACTIVE INGREDIENTS: MENTHOL 15 mg/1 g; CAPSAICIN 0.25 mg/1 g
INACTIVE INGREDIENTS: CARBOMER INTERPOLYMER TYPE A (ALLYL SUCROSE CROSSLINKED); ALOE VERA LEAF; CHAMAEMELUM NOBILE WHOLE; WATER; ARNICA MONTANA FLOWER; ASCORBYL PALMITATE; CALENDULA OFFICINALIS FLOWER; CENTAUREA CYANUS FLOWER; CHAMOMILE; CORIANDER; EMU OIL; ETHYLHEXYLGLYCERIN; WITCH HAZEL; SUNFLOWER OIL; HYPERICUM PERFORATUM WHOLE; LAMIUM ALBUM WHOLE; DIMETHYL SULFONE; PHENOXYETHANOL; SALIX ALBA BARK; SODIUM LAURYL SULFATE; SORBITOL; TROLAMINE; TANACETUM PARTHENIUM WHOLE; FD&C BLUE NO. 1; FD&C YELLOW NO. 5

BLUE SPRING Foot & Leg Comfort Cream with Pain Relief

Active Ingredient:

Menthol, USP (1.5%), Capsaicin (0.025%)

Purpose:

- Topical Analgesic

Uses:

- Temporary relief of minor aches and pains of muscles and joints.

Warnings:

- For external use only.

Do not use

on wounded, damaged or irritated skin.

When using this product

avoid contact with eyes or mucous membranes, do not bandaged tightly.

Stop use and ask a doctor if

- you experience a rash and/or a reaction, condition worsens, or if symptoms persist for more than 10 days or clear up and occur again within a few days.

If Pregnant or Breast-Feeding

ask a health professional before use.

Keep out of reach of children.

- If swallowed, get medical help or contact a Poison Control Center right away.

Directions:

- For adults and children 2 years of age and older: apply to affected area not more than 3 or 4 times a day. Consult a doctor before using for children under 2 years of age.

Inactive Ingredients:

Acrylates/C10-30 Alkyl Acrylate Crosspolymer, Aloe Barbadensis Leaf (Aloe Vera Gel) Juice, Anthemis Nobilis (Roman Chamomile) Oil, Aqua (Deionized Water), Arnica Montana Flower Extract, Ascorbyl Palmitate (Vitamin C), Calendula Officinalis Extract, Centaurea Cyanus (Cornflower) Extrat, Chamomilla Recutita (Chamomile) Extract, Coriandrum Satiyum (Coriander) Oil, Emu Oil, Ethylhexylglycerin, Hamamelis Virgiana (Witch Hazel), Helianthus Annuus (Sunflower) Oil, Hypericum Perforatum (St. John's Wort), Lamium Album (White Nettle) Extract, Methylsulfony Methane (MSM), Parfum (Fragrance), Phenoxyethanol, Salix Alba (Willow) Bark Extract, SD-Alcohol 40B, Sodium Lauryl Sulfate, Sorbitol, Tillia Cordata (Linden) Bark Extarct, Triethanolamine, Fever Few Extract, FD&C Blue#1, FD&C Yellow #5.

Questions or Comments?

1.800.452.3700 or www.bluespringwellness. com